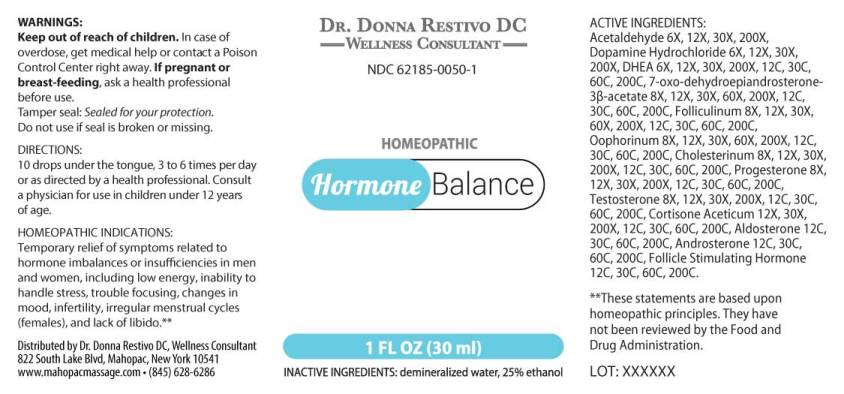 DRUG LABEL: Hormone Balance
NDC: 62185-0050 | Form: LIQUID
Manufacturer: Dr. Donna Restivo DC
Category: homeopathic | Type: HUMAN OTC DRUG LABEL
Date: 20250523
DEA Schedule: CIII

ACTIVE INGREDIENTS: ACETALDEHYDE 6 [hp_X]/1 mL; DOPAMINE HYDROCHLORIDE 6 [hp_X]/1 mL; 7-OXODEHYDROEPIANDROSTERONE 3-ACETATE 6 [hp_X]/1 mL; ESTRONE 8 [hp_X]/1 mL; SUS SCROFA OVARY 8 [hp_X]/1 mL; CHOLESTEROL 8 [hp_X]/1 mL; PROGESTERONE 8 [hp_X]/1 mL; TESTOSTERONE 8 [hp_X]/1 mL; CORTISONE ACETATE 12 [hp_X]/1 mL; ALDOSTERONE 12 [hp_C]/1 mL; ANDROSTERONE 12 [hp_C]/1 mL; FOLLITROPIN 12 [hp_C]/1 mL
INACTIVE INGREDIENTS: WATER; ALCOHOL

Drug Facts:

ACTIVE INGREDIENTS:

Acetaldehyde 6X, 12X, 30X, 200X, Dopamine Hydrochloride 6X, 12X, 30X, 200X, DHEA (Dehydroepiandrosterone) 6X, 12X, 30X, 200X, 12C, 30C, 60C, 200C, 7-Oxo-Dehydroepiandrosterone 3-Acetate 8X, 12X, 30X, 60X, 200X, 12C, 30C, 60C, 200C, Folliculinum 8X, 12X, 30X, 60X, 200X, 12C, 30C, 60C, 200C, Oophorinum (Suis) 8X, 12X, 30X, 60X, 200X, 12C, 30C, 60C, 200C, Cholesterinum 8X, 12X, 30X, 200X, 12C, 30C, 60C, 200C,Progesterone 8X, 12X, 30X, 200X, 12C, 30C, 60C, 200C, Testosterone 8X, 12X, 30X, 200X, 12C, 30C, 60C, 200C, Cortisone Aceticum 12X, 30X, 200X, 12C, 30C, 60C, 200C, Aldosterone 12C, 30C, 60C, 200C, Androsterone 12C, 30C, 60C, 200C, Follicle Stimulating Hormone 12C, 30C, 60C, 200C.

HOMEOPATHIC INDICATIONS:

Temporary relief of symptoms related to hormone imbalances or insufficiencies in men and women, including low energy, inability to handle stress, trouble focusing, changes in mood, infertility, irregular menstrual cycles (females) and lack of libido.**

**These statements are based upon traditional homeopathic principles. They have not been reviewed by the Food and Drug Administration.

WARNINGS:

Keep out of reach of children. In case of overdose, get medical help or contact or a Poison Control Center right away.

If pregnant or breast-feeding, ask a health professional before use.

Tamper seal: "Sealed for Your Protection." Do not use if seal is broken or missing.

Keep out of reach of children. In case of overdose, get medical help or contact or a Poison Control Center right away.

DIRECTIONS:

10 drops under the tongue, 3 to 6 times per day or as directed by a health professional. Consult a physician for use in children under 12 years of age.

HOMEOPATHIC INDICATIONS:

Temporary relief of symptoms related to hormone imbalances or insufficiencies in men and women, including low energy, inability to handle stress, trouble focusing, changes in mood, infertility, irregular menstrual cycles (females) and lack of libido.**

**These statements are based upon traditional homeopathic principles. They have not been reviewed by the Food and Drug Administration.

INACTIVE INGREDIENTS:

demineralized water, 25% ethanol.

QUESTIONS:

Distributed by Dr. Donna Restivo DC, Wellness Consultant
822 South Lake Blvd, Mahopac, New York 10541
www.mahopacmassage.com • (845) 628-6286

PACKAGE LABEL DISPLAY:

DR. DONNA RESTIVO DC
WELLNESS CONSULTANT
NDC 62185-0041-1
HOMEOPATHIC
Hormone Balance
1 FL OZ (30 ml)